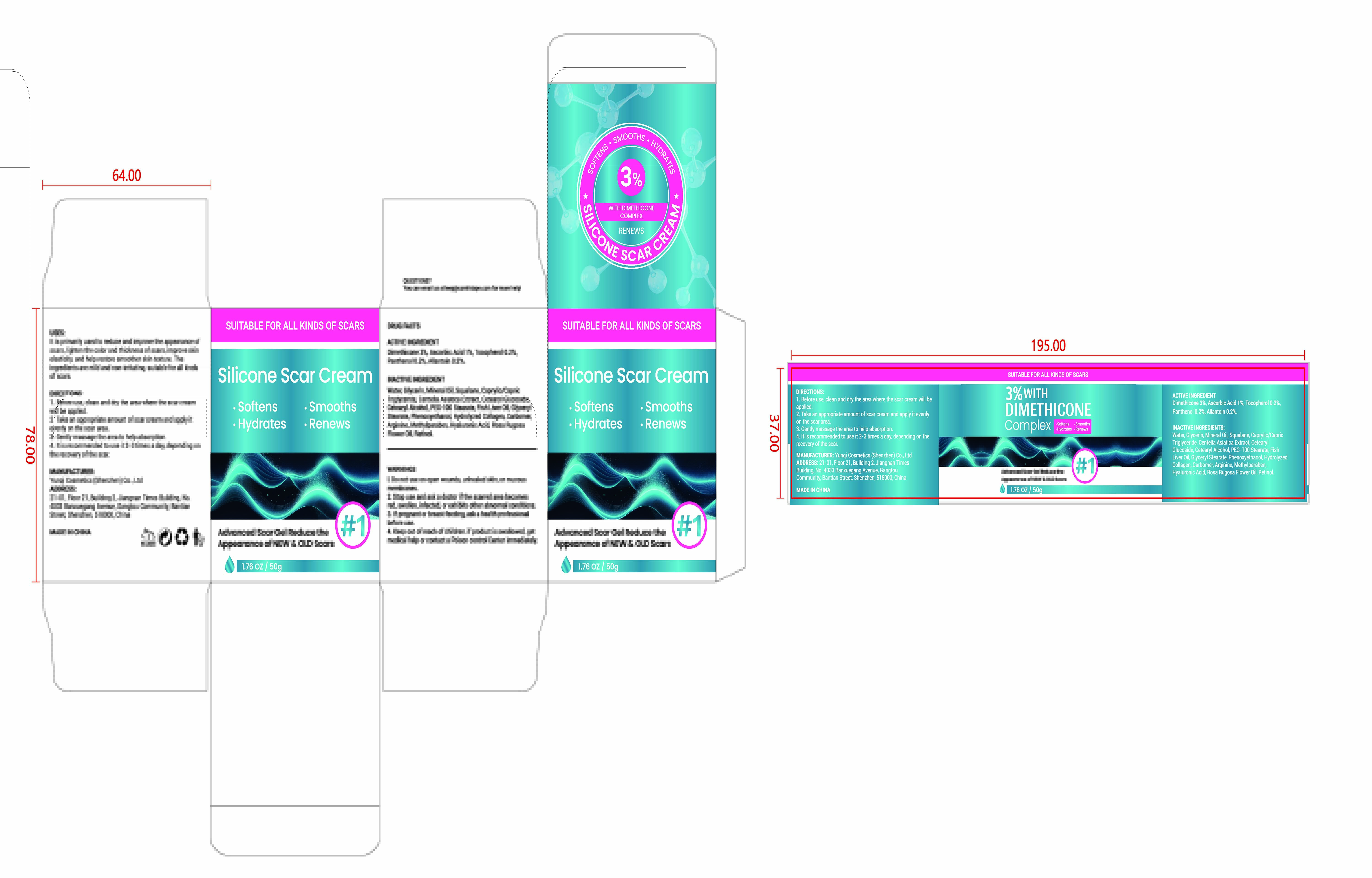 DRUG LABEL: Silicone Scar Cream
NDC: 84763-007 | Form: CREAM
Manufacturer: Yunqi Cosmetics (Shenzhen) Co., Ltd
Category: otc | Type: HUMAN OTC DRUG LABEL
Date: 20250617

ACTIVE INGREDIENTS: ASCORBIC ACID 1 g/100 g; PANTHENOL 0.2 g/100 g; ALLANTOIN 0.2 g/100 g; TOCOPHEROL 0.2 g/100 g; DIMETHICONE 3 g/100 g
INACTIVE INGREDIENTS: CENTELLA ASIATICA TRITERPENOIDS; CETEARYL ALCOHOL; GLYCERYL STEARATE; SQUALANE; CETEARYL GLUCOSIDE; HYDROLYZED ELASTIN; HYALURONIC ACID; ROSA CANINA FLOWER OIL; RETINOL; CARBOMER; WATER; TRICAPRIN; PHENOXYETHANOL; MINERAL OIL; GLYCERIN; FISH LIVER OIL; ARGININE; METHYLPARABEN; PEG-100 STEARATE

84763-007 Silicone Scar Cream

ACTIVE INGREDIENT

Dimethicone 3%
Ascorbic Acid 1%
Tocopherol 0.2%
Panthenol 0.2%
Allantoin 0.2%

PURPOSE

Advanced Scar Gel Reduce theAppearance of NEW & OLD Scars

INDICATIONS AND USAGE

It is primarily used to reduce and improve the appearance ofscars, lighten the color and thickness of scars, improve skinelasticity, and help restore smoother skin texture. Theingredients are mild and non-irritating, suitable for all kindsof scars.

WARNINGS

For external use only

DO NOT USE

1. Do not use on open wounds, unhealed skin, or mucousmembranes.

WHEN USING

3. lf pregnant or breast-feeding, ask a health professionalbefore use.
4. Keep out of reach of children. if product is swallowed, getmedical help or contact a Poison control Center immediately.

STOP USE

2. Stop use and ask a doctor if the scarred area becomesred, swollen, infected, or exhibits other abnormal conditions.

Keep out of reach of children. if product is swallowed, getmedical help or contact a Poison control Center immediately.

DOSAGE AND ADMINISTRATION

1. Before use, clean and dry the area where the scar creamwill be applied.
2. Take an appropriate amount of scar cream and apply itevenly on the scar area.
3. Gently massage the area to help absorption.
4. lt is recommended to use it 2-3 times a day, depending onthe recovery of the scar.

INACTIVE INGREDIENT

Water
Glycerin
Mineral Oil
Squalane
Caprylic/Capric Triglyceride
Centella Asiatica Extract
Cetearyl Glucoside
Cetearyl Alcohol
PEG-100 Stearate
Fish Liver Oil
Glyceryl Stearate
Phenoxyethanol
Hydrolyzed Collagen
Carbomer
Arginine
Methylparaben
Hyaluronic Acid
Rosa Rugosa Flower Oil
Retinol